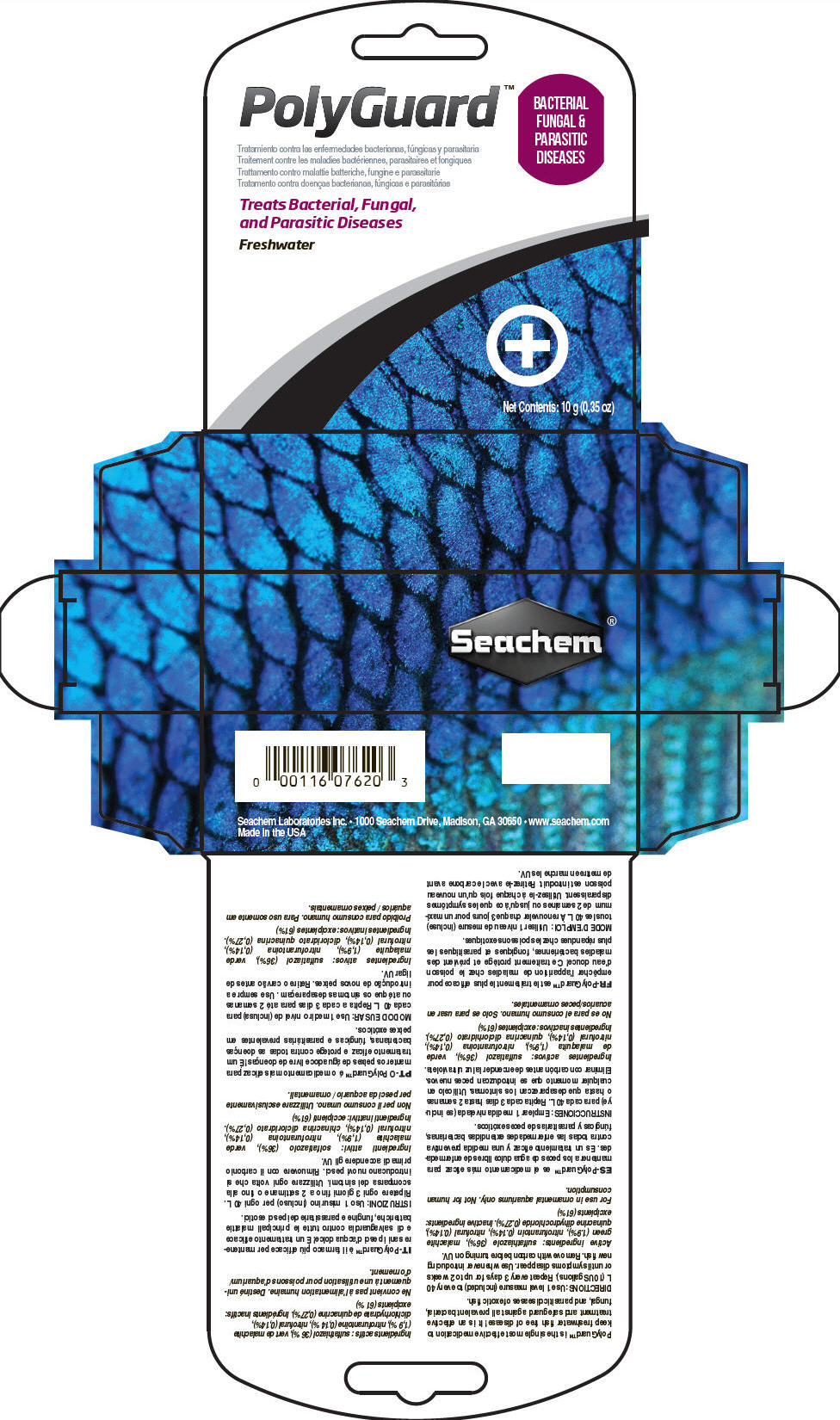 DRUG LABEL: Polyguard
NDC: 55999-077 | Form: POWDER
Manufacturer: Seachem Laboratories Inc.
Category: animal | Type: OTC ANIMAL DRUG LABEL
Date: 20180724

ACTIVE INGREDIENTS: Sulfathiazole 364 mg/1 g; Malachite Green 19 mg/1 g; Nitrofurantoin 1 mg/1 g; Quinacrine 2 mg/1 g; Nitrofurazone 1 mg/1 g

PolyGuard™

VETERINARY INDICATIONS

PolyGuard™ is the single most effective medication to keep freshwater fish free of disease! It is an effective treatment and safeguard against all prevalent bacterial, fungal, and parasitic diseases of exotic fish.

DOSAGE AND ADMINISTRATION

DIRECTIONS: Use 1 level measure (included) to every 40 L (10 USgallons). Repeat every 3 days for up to 2 weeks or until symptoms disappear. Use whenever introducing new fish. Remove with carbon before turning on UV.

Active ingredients: sulfathiazole (36%), malachite green (1.9%), nitrofurantoin (0.14%), nitrofural (0.14%), quinacrine dihydrochloride (0.27%). Inactive ingredients: excipients (61%)

SAFE HANDLING WARNING

For use in ornamental aquariums only. Not for human consumption.

Seachem Laboratories Inc. • 1000 Seachem Drive, Madison, GA 30650 • www.seachem.com

Made in the USA

PRINCIPAL DISPLAY PANEL - 10 g Vial Carton

PolyGuard™

BACTERIAL
FUNGAL &
PARASITIC
DISEASES

Treats Bacterial, Fungal,
and Parasitic Diseases

Freshwater

Net Contents: 10 g (0.35 oz)

Seachem®